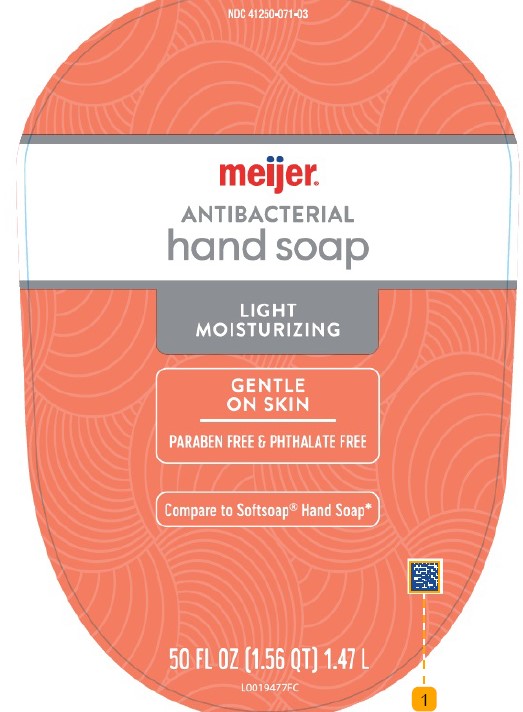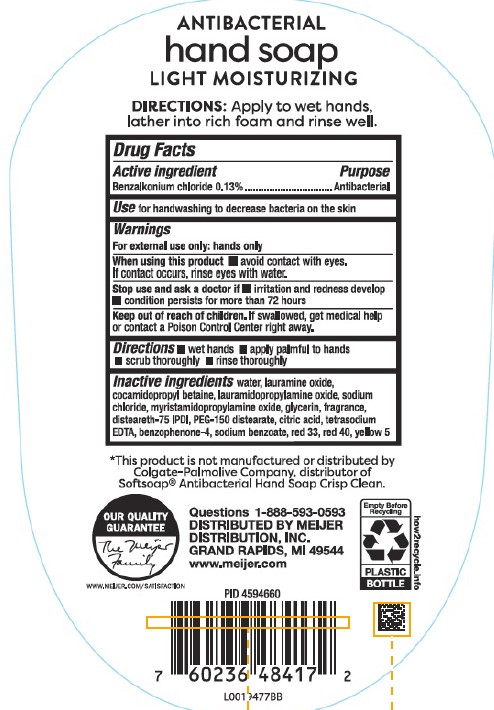 DRUG LABEL: Moisturizing Antibacterial
NDC: 41250-071 | Form: SOAP
Manufacturer: Meijer, Inc.
Category: otc | Type: HUMAN OTC DRUG LABEL
Date: 20260219

ACTIVE INGREDIENTS: BENZALKONIUM CHLORIDE 1.3 mg/1 mL
INACTIVE INGREDIENTS: WATER; LAURAMINE OXIDE; COCAMIDOPROPYL BETAINE; LAURAMIDOPROPYLAMINE OXIDE; SODIUM CHLORIDE; MYRISTAMIDOPROPYLAMINE OXIDE; GLYCERIN; DISTEARETH-75 ISOPHORONE DIISOCYANATE; PEG-150 DISTEARATE; CITRIC ACID MONOHYDRATE; EDETATE SODIUM; SULISOBENZONE; SODIUM BENZOATE; D&C RED NO. 33; FD&C RED NO. 40; FD&C YELLOW NO. 5

Meijer 279.003/279AE
Light Moisturizing Antibacterial Hand Soap

Claims

ANTIBACTERIAL

hand soap

LIGHT MOISTURIZING

DIRECTIONS: Apply to wet hands, lather into rich foam and rinse well.

Active ingredient

Benzalkonium chloride 0.13%

Purpose

Antibacterial

Use

for handwashing to decrease bacteria on the skin

Warnings

For external use only: hands only

When using this product

- avoid contact with eyes. If contact occurs, rinse eyes thoroughly with water

Stop use and ask a doctor if

- irritation and redness develop
- condition persists for more than 72 hours

Keep out of reach of children.

If swallowed, get medical help or contact a Poison Control Center right away.

Directions

- wet hands
- apply palmful to hands
- scrub thoroughly
- rinse thoroughly

Inactive ingredients

water, lauramine oxide, cocamidopropyl betaine, lauramidopropylamine oxide, sodium chloride, myristamidopropylamine oxide, glycerin, fragrance, disteareth-75 IPDI, PEG-150 distearate, citric acid, tetrasodium EDTA, benzophenone-4, sodium benzoate, red 33, red 40, yellow 5

Disclaimer

*This product is not manufactured or distributed by Colgate-Palmolive Company, distributor of Softsoap Antibacterial Hand Soap Crisp Clean.

Adverse reaction

Questions 1-888-593-0593

DISTRIBUTED BY MEIJER DISTRIBUTION, INC.

GRAND RAPIDS, MI 49544

www.meijer.com

OUR QUALITY GUARANTEE

The Meijer Family

www.meijer.com/satisfaction

Empty Before Recycling

PLASTIC BOTTLE

how2recycle.info

principal display panel

NDC 41250-071-03

meijer

ANTIBACTERIAL

hand soap

LIGHT MOISTURIZING

GENTLE ON SKIN

PARABEN FREE & PHTHALATE FREE

Compare to Softsoap Hand Soap*

50 FL OZ (1.56 QT) 1.47 L